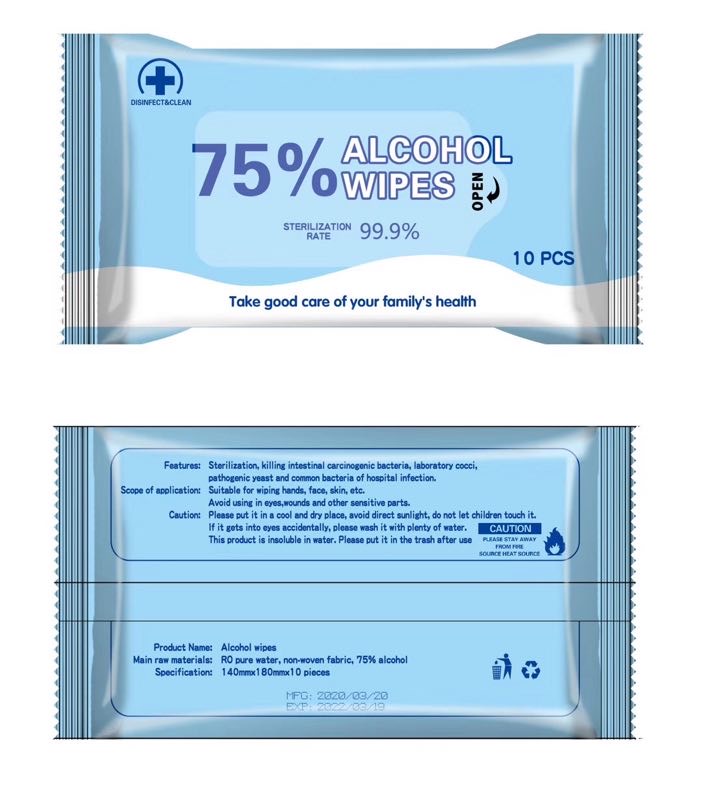 DRUG LABEL: Nutrivsta Alcohol Wipes
NDC: 78369-535 | Form: CLOTH
Manufacturer: WENZHOU GUANGSEN PAPER CO., LTD.
Category: otc | Type: HUMAN OTC DRUG LABEL
Date: 20200613

ACTIVE INGREDIENTS: ALCOHOL 75 mL/100 1
INACTIVE INGREDIENTS: WATER

WENZHOU GUANGSEN PAPER CO., LTD.

Active Ingredient

Ethyl Alcohol 75% v/v

Purpose

Ethyl Alcohol Antiseptic

Use

Helps reduce bacteria that potentially can cause disease.

Warnings

For external use only. Flammable. Keep away from heat or flame.

Do not use

- in children less than 2 months of age.
- on open skin wounds.

When using this product

keep out of eyes, ears, and mouth. In case of contact with eyes, rinse eyes thoroughly with water.

Stop use

Stop use and ask a doctor if irritation or rash occurs. These may be signs of a serious condition.

Keep out of reach of children.

If swallowed, get medical help or contact a Poison Control Center right away.

Directions

- Open the package lid and wipe skin until dry.
- Supervise children under 6 years of age when using this product to avoid swallowing.

Other information

- Store between 15-30C (59-86F)
- Avoid freezing and excessive heat above 40C (104F)

Manufactured by WENZHOU GUANGSEN PAPER CO., LTD.
Building 2, Qiancang Dongjiang Industrial Zone, Pingyang City, Wenzhou, Zhejiang, China 51000
Distributed by Nutrivsta LLC
2299 Huntington Dr. #D
San Marino, CA 91108
Phone: (626)356-2932
Email: 23laurayang@gmail.com

Inactive ingredients

WATER